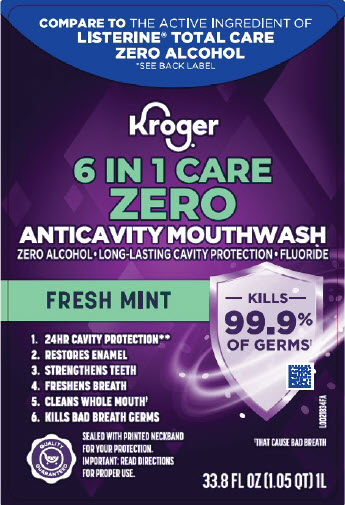 DRUG LABEL: Anticavity
NDC: 59450-971 | Form: RINSE
Manufacturer: The Kroger Co.
Category: otc | Type: HUMAN OTC DRUG LABEL
Date: 20260227

ACTIVE INGREDIENTS: SODIUM FLUORIDE 0.1 mg/1 mL
INACTIVE INGREDIENTS: SODIUM BENZOATE; WATER; SORBITOL; PROPYLENE GLYCOL; POLOXAMER 407; SODIUM LAURYL SULFATE; PHOSPHORIC ACID; EUCALYPTOL; METHYL SALICYLATE; THYMOL; SACCHARIN SODIUM; MENTHOL, UNSPECIFIED FORM; SODIUM PHOSPHATE, DIBASIC, ANHYDROUS; SUCRALOSE; SPEARMINT OIL; PEPPERMINT OIL; FD&C RED NO. 40; FD&C BLUE NO. 1

Kroger 971.001/971AB
Anticavity Fluoride Rinse

Active Ingredient

Sodium fluoride 0.02% (0.01% w/v fluoride ion)

Purpose

Anticavity

Use

aids in the prevention of dental cavities

Warning

for this product

Keep out of Reach of Children

If more than used for rinsing is accidentally swallowed, get medical help or contact a Poison Control Center right away.

Directions

Adults and children 6 years of age and older:

- use twice daily after brushing your teeth with a toothpaste
- vigorously swish 10 mL of rinse between your teeth for 1 minute and then spit out.
- do not swallow the rinse
- do not eat or drink for 30 minutes after rinsing
- instruct children under 12 years of age in good rinsing habits (to minimize swallowing)
- supervise children as necessary until capable of using without supervision

children under 6 years of age: consult a dentist or doctor

Other information

- store at controlled room temperature 20⁰ - 25⁰ C (68⁰ - 77⁰ F)
- cold weather may temporarily cloud this product

Inactive ingredients

water, sorbitol, propylene glycol, poloxamer 407, sodium lauryl sulfate, flavor, sodium benzoate, phosphoric acid, eucalyptol, methyl salicylate, thymol, sodium saccharin, menthol, disodium phosphate, sucralose, Mentha viridis (spearmint) leaf oil, Mentha piperita (peppermint) oil, red 40, blue 1

Questions or comments?

Call 1-800-632-6900

Disclaimer

*LISTERINE IS A REGISTERED TRADEMARK OF KENVUE, INC.

**WHEN USED 2X DAILY

Adverse Reaction

PROUDLY DISTRIBUTED BY THE KROGER CO.

CINCINNATI, OHIO 45202

MADE IN USA WITH DOMESTIC AND FOREIGN COMPONENTS

‡THIS PRODUCT IS NOT INTENDED TO REPLACE BRUSHING OR FLOSSING.

QUALITY GUARANTEED

Quality Guaranteed

Kroger.com/guarantee

800-632-6900

principal panel display

COMPARE TO THE ACTIVE INGREDIENT OF LISTERINE TOTAL CARE ZERO ALCOHOL

*SEE BACK LABEL

Kroger

6 IN 1 CARE

ZERO

ANTICAVITY MOUTHWASH

ZERO ALCOHOL • LONG-LASTING CAVITY PROTECTION • FLUORIDE

FRESH MINT

KILLS 99.9% OF GERMS†

†THAT CAUSE BAD BREATH

1. 24HR CAVITY PROTECTION**
2. RESTORES ENAMEL
3. STRENGTHENS TEETH
4. FRESHENS BREATH
5. CLEANS WHOLE MOUTH†
6. KILLS BAD BREATH GERMS

QUALITY GUARANTEED

SEALED WITH PRINTED NECKBAND FOR YOUR PROTECTION.

IMPORTANT: READ DIRECTIONS FOR PROPER USE.

33.8 FL OZ (1.05 QT) 1L